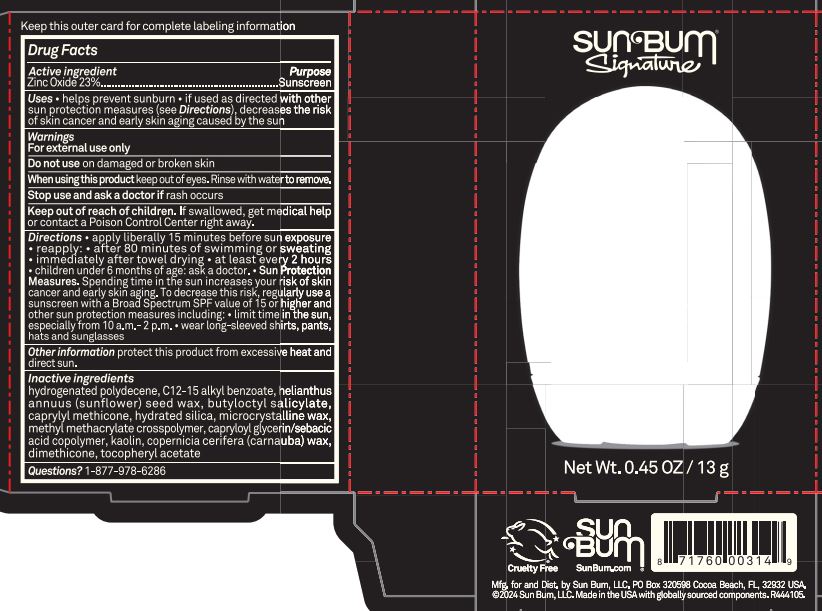 DRUG LABEL: Sun Bum Signature High Performance Mineral Sunscreen Face Stick 30
NDC: 69039-820 | Form: STICK
Manufacturer: Sun Bum, LLC
Category: otc | Type: HUMAN OTC DRUG LABEL
Date: 20250821

ACTIVE INGREDIENTS: ZINC OXIDE 230 mg/1 g
INACTIVE INGREDIENTS: METHYL METHACRYLATE; CAPRYLOYL GLYCERIN/SEBACIC ACID COPOLYMER (2000 MPA.S); CAPRYLYL METHICONE; HYDRATED SILICA; KAOLIN; HELIANTHUS ANNUUS (SUNFLOWER) SEED WAX; DIMETHICONE; MICROCRYSTALLINE WAX; COPERNICIA CERIFERA (CARNAUBA) WAX; .ALPHA.-TOCOPHEROL ACETATE; HYDROGENATED POLYDECENE (1500 CST); C12-15 ALKYL BENZOATE; BUTYLOCTYL SALICYLATE

Sun Bum Signature High Performance Mineral Sunscreen Face Stick 30

Active Ingredients

Zinc Oxide 23%

Purpose

Sunscreen

Uses

• helps prevent sunburn • if used as directed with other sun protection measures, (see Directions) decreases the risk of skin cancer and early skin aging caused by the sun

Warnings

For external use only.

Do not use on damaged or broken skin

When using this product keep out of eyes. Rinse with water to remove.

Stop use and ask a doctor if rash occurs

Keep out of reach of children. If swallowed, get medical help or contact a Poison Control Center immediately.

Warnings

Keep Out Of Reach Of Children

Directions

• apply liberally 15 minutes before sun exposure

• reapply: • after 80 minutes of swimming or sweating • immediately after towel drying • at least every 2 hours

• children under 6 months of age: ask a doctor

• Sun Protection Measures. Spending time in the sun increases your risk of skin cancer and early skin aging. To decrease this risk, regularly use a sunscreen with a Broad Spectrum SPF value of 15 or higher and other sun protection measures including:

• limit time in the sun, especially from 10 a.m.- 2 p.m.

• wear long-sleeved shirts, pants, hats and sunglasses

Directions

• apply liberally 15 minutes before sun exposure

Other Information

protect this product from excessive heat and direct sun

Inactive Ingredients

hydrogenated polydecene, C12-15 alkyl benzoate, helianthus annuus (sunflower) seed wax, butyloctyl salicylate, caprylyl methicone, hydrated silica, microcrystalline wax, methyl methacrylate crosspolymer, capryloyl glycerin/sebacic acid copolymer, kaolin, copernicia cerifera (carnauba) wax, dimethicone, tocopheryl acetate

Questions?

1-877-978-6286